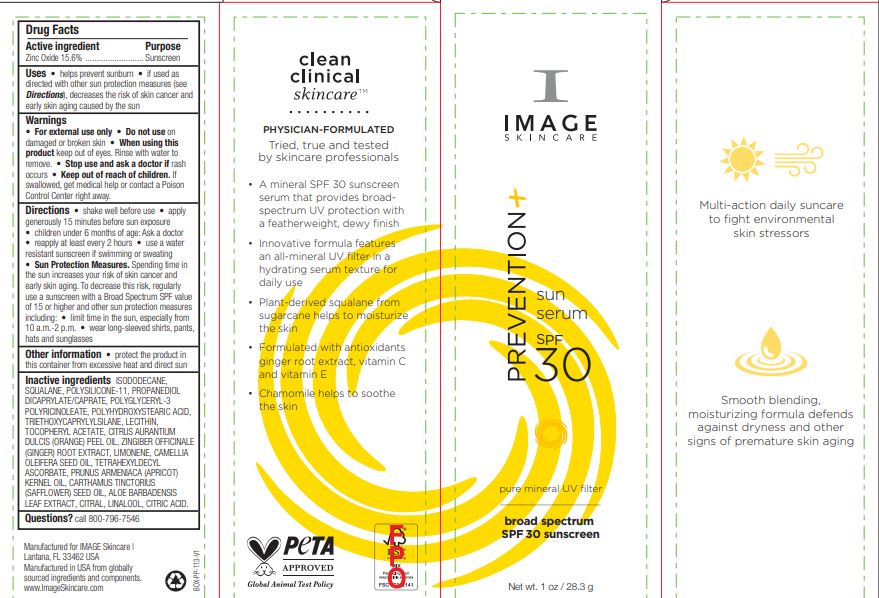 DRUG LABEL: Prevention Sun Serum SPF30
NDC: 62742-4225 | Form: CREAM
Manufacturer: Allure Labs
Category: otc | Type: HUMAN OTC DRUG LABEL
Date: 20241209

ACTIVE INGREDIENTS: ZINC OXIDE 15.6 g/100 g
INACTIVE INGREDIENTS: ORANGE OIL; GINGER; LIMONENE, (+)-; TETRAHEXYLDECYL ASCORBATE; CITRAL; LINALOOL, (+/-)-; ISODODECANE; DIMETHICONE/VINYL DIMETHICONE CROSSPOLYMER (SOFT PARTICLE); SAFFLOWER OIL; ALOE VERA LEAF; CITRIC ACID MONOHYDRATE; PROPANEDIOL DICAPRYLATE/CAPRATE; POLYHYDROXYSTEARIC ACID (2300 MW); TRIETHOXYCAPRYLYLSILANE; SQUALANE; POLYGLYCERYL-3 PENTARICINOLEATE; CAMELLIA OIL; LECITHIN, SOYBEAN; .ALPHA.-TOCOPHEROL ACETATE; APRICOT KERNEL OIL

Drug Facts

Active ingredient

Zinc Oxide 15.6%

Purpose

Sunscreen

Uses

Helps prevent sunburn • if used as directed with other sun protection measures (see Directions), decreases the risk of skin cancer and early skin aging caused by the sun

Warnings

For external use only

Do not use on damaged or broken skin

When using this product keep out of eyes. Rinse with water to remove

Stop use and ask a doctor if rash occurs

Keep out of reach of children. If swallowed, get medical help or contact a Poison Control Center right away

DOSAGE AND ADMINISTRATION

Shake well before use • apply generously 15 minutes before sun exposure • children under 6 months of age: Ask a doctor • reapply at least every 2 hours • use a water resistant sunscreen if swimming or sweating • Sun Protection Measures. Spending time in the sun increases your risk of skin cancer and early skin aging. To decrease this risk, regularly use a sunscreen with a Broad Spectrum SPF value of 15 or higher and other sun protection measures including: • limit time in the sun, especially from 10 a.m.-2 p.m. • wear long-sleeved shirts, pants, hats and sunglasses

Other information • protect the product in this container from excessive heat and direct sun

Inactive ingredients:

ISODODECANE, SQUALANE, POLYSILICONE-11, PROPANEDIOL DICAPRYLATE/CAPRATE, POLYGLYCERYL-3 POLYRICINOLEATE, POLYHYDROXYSTEARIC ACID, TRIETHOXYCAPRYLYLSILANE, LECITHIN, TOCOPHERYL ACETATE, CITRUS AURANTIUM DULCIS (ORANGE) PEEL OIL ZINGIBER OFFICINALE (GINGER) ROOT EXTRACT, LIMONENE, CAMELLIA OLEIFERA SEED OIL, TETRAHEXYLDECYL ASCORBATE, PRUNUS ARMENIACA (APRICOT) KERNEL OIL, CARTHAMUS TINCTORIUS (SAFFLOWER) SEED OIL, ALOE BARBADENSIS LEAF EXTRACT, CITRAL, LINALOOL, CITRIC ACID.